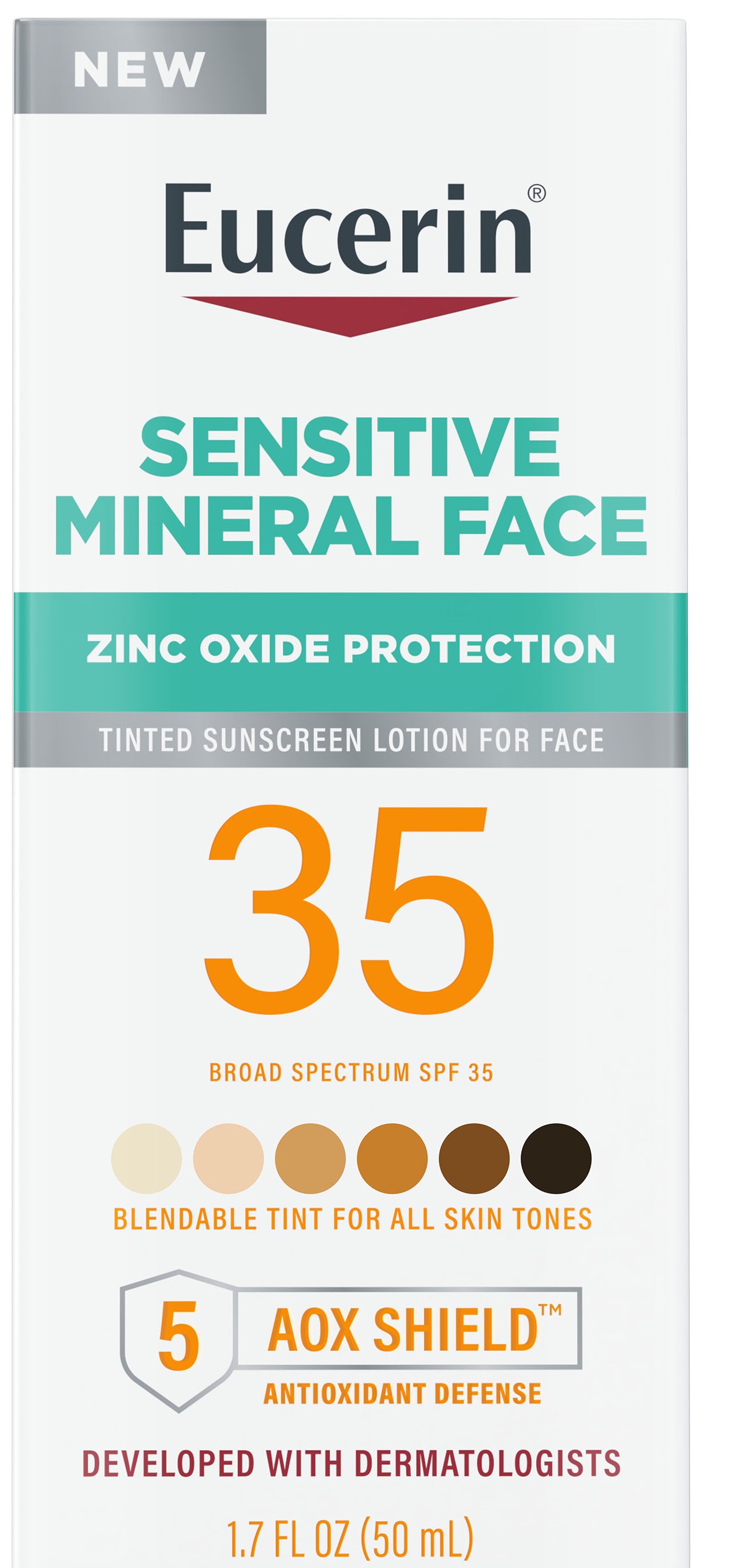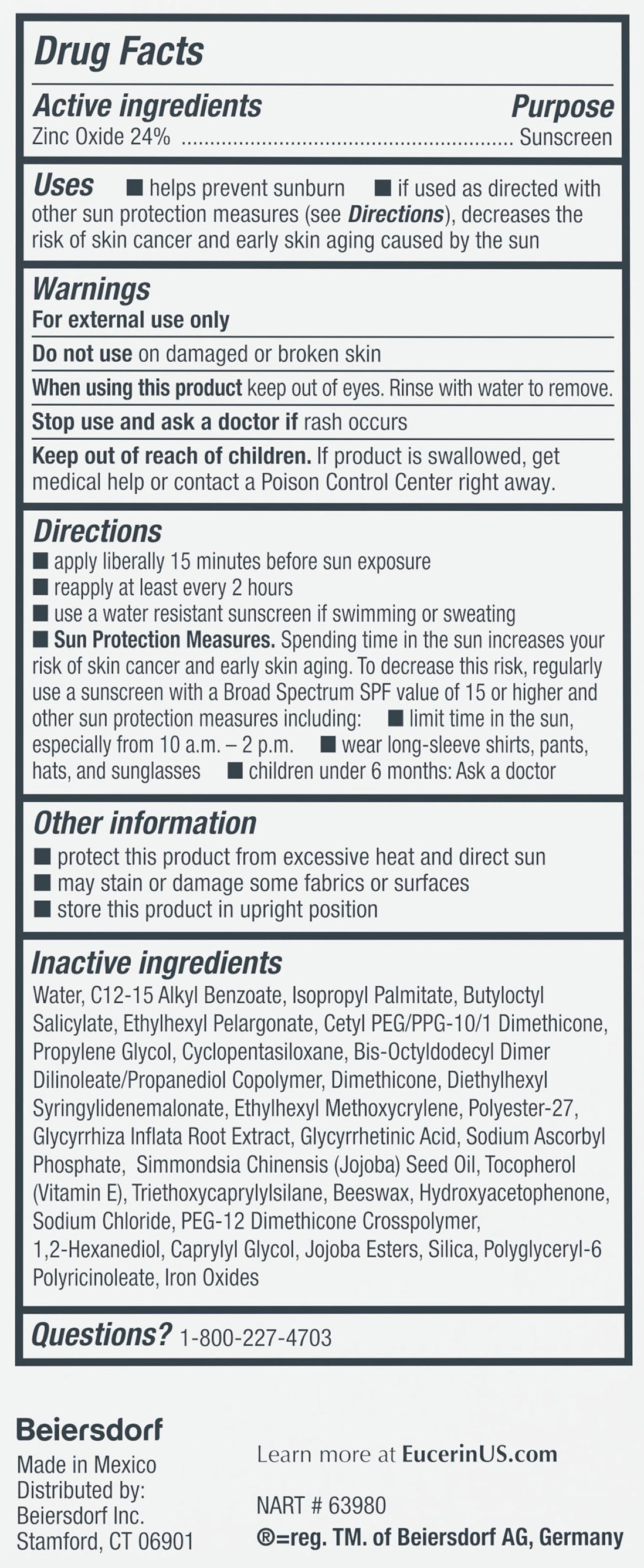 DRUG LABEL: Eucerin Sensitive Mineral Face Sunscreen SPF 35
NDC: 66800-7000 | Form: LOTION
Manufacturer: Beiersdorf Inc
Category: otc | Type: HUMAN OTC DRUG LABEL
Date: 20251231

ACTIVE INGREDIENTS: ZINC OXIDE 24 g/100 g
INACTIVE INGREDIENTS: GLYCYRRHIZA INFLATA ROOT; SODIUM ASCORBYL PHOSPHATE; TOCOPHEROL; TRIETHOXYCAPRYLYLSILANE; SYNTHETIC BEESWAX; SODIUM CHLORIDE; BIS-OCTYLDODECYL DIMER DILINOLEATE/PROPANEDIOL COPOLYMER; JOJOBA OIL; WATER; ALKYL (C12-15) BENZOATE; ISOPROPYL PALMITATE; CETYL PEG/PPG-10/1 DIMETHICONE (HLB 2); PEG-12 DIMETHICONE/PPG-20 CROSSPOLYMER; TITANIUM DIOXIDE; BUTYLOCTYL SALICYLATE; ETHYLHEXYL PELARGONATE; DIETHYLHEXYL SYRINGYLIDENEMALONATE; ETHYLHEXYL METHOXYCRYLENE; POLYESTER-7; FERROUS OXIDE; DIMETHICONE; HYDROXYACETOPHENONE; PROPYLENE GLYCOL; CYCLOMETHICONE 5; 1,2-HEXANEDIOL; CAPRYLYL GLYCOL; HYDROLYZED JOJOBA ESTERS (ACID FORM); POLYGLYCERYL-6 POLYRICINOLEATE; ENOXOLONE

Eucerin Sensitive Mineral Face Lotion SPF 35

Active ingredient

Zinc Oxide 24%

Purpose

Sunscreen

Uses

■ helps prevent sunburn

■ if used as directed with other sun protection measures (see Directions), decreases the risk of skin cancer and early skin aging caused by the sun

Warnings

For external use only

Do not useon damaged or broken skin

WHEN USING

When using this productkeep out of eyes. Rinse with water to remove.

Stop use and ask a doctor ifrash occurs

Keep out of reach of children.If product is swallowed, get medical help or contact a Poison Control Center right away.

Directions

■ apply liberally 15 minutes before sun exposure

■ reapply at least every 2 hours

■ use a water resistant sunscreen if swimming or sweating

■ Sun Protection Measures.Spending time in the sun increases your risk of skin cancer and early skin aging. To decrease this risk, regularly use a sunscreen with a Broad Spectrum SPF value of 15 or higher and other sun protection measures including:

■ limit time in the sun, especially from 10 a.m. – 2 p.m.

■ wear long-sleeve shirts, pants, hats, and sunglasses

■ children under 6 months: Ask a doctor

Other information

■ protect this product from excessive heat and direct sun

■ may stain or damage some fabrics or surfaces

■ store this product in upright position

Inactive ingredients

Water, C12-15 Alkyl Benzoate, Isopropyl Palmitate, Butyloctyl Salicylate, Ethylhexyl Pelargonate, Cetyl PEG/PPG-10/1 Dimethicone, Propylene Glycol, Cyclopentasiloxane, Bis-Octyldodecyl Dimer Dilinoleate/Propanediol Copolymer, Dimethicone, Diethylhexyl Syringylidenemalonate, Ethylhexyl Methoxycrylene, Polyester-27, Glycyrrhiza Inflata Root Extract, Glycyrrhetinic Acid, Sodium Ascorbyl Phosphate, Simmondsia Chinensis (Jojoba) Seed Oil, Tocopherol (Vitamin E), Triethoxycaprylylsilane, Beeswax, Hydroxyacetophenone, Sodium Chloride, PEG-12 Dimethicone Crosspolymer, 1,2-Hexanediol, Caprylyl Glycol, Jojoba Esters, Silica, Polyglyceryl-6 Polyricinoleate, Iron Oxides

Questions?

1-800-227-4703

PACKAGE LABEL

Eucerin®

Sensitive Mineral Face

Zinc Oxide Protection

Tinted Sunscreen Lotion For Face

35

Broad Spectrum SPF 35

Blendable Tint For All Skin Tones

5 AOX Shield™

Antioxidant Defense

Developed With Dermatologists